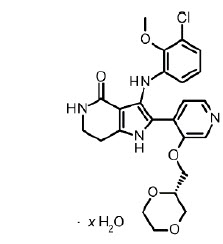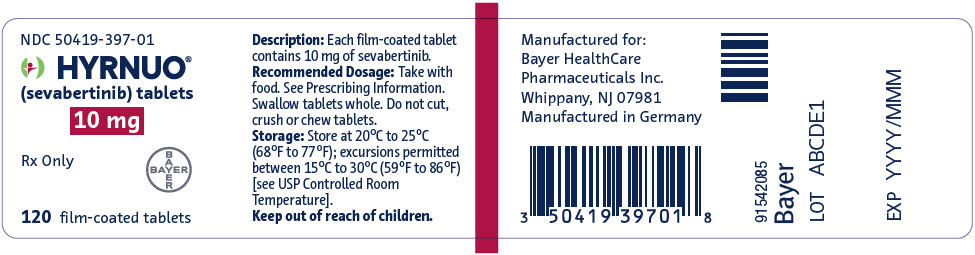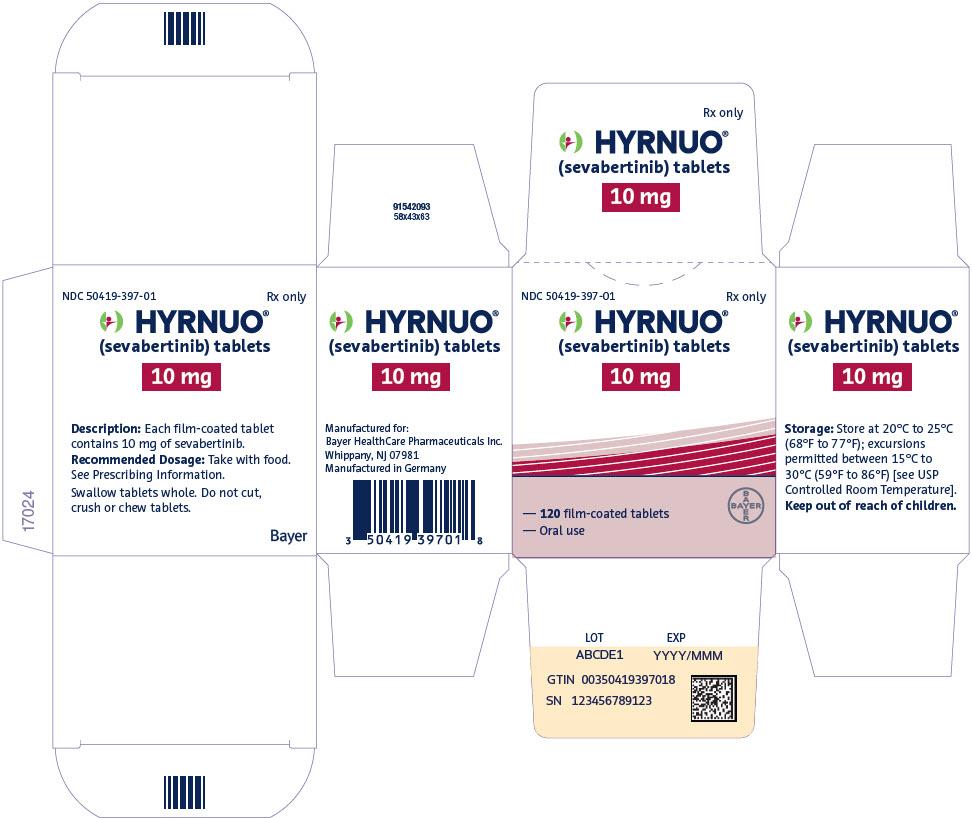 DRUG LABEL: HYRNUO
NDC: 50419-397 | Form: TABLET, FILM COATED
Manufacturer: Bayer HealthCare Pharmaceuticals Inc.
Category: prescription | Type: HUMAN PRESCRIPTION DRUG LABEL
Date: 20251203

ACTIVE INGREDIENTS: SEVABERTINIB 10 mg/1 1
INACTIVE INGREDIENTS: MICROCRYSTALLINE CELLULOSE; CROSPOVIDONE, UNSPECIFIED; LACTOSE MONOHYDRATE; MAGNESIUM STEARATE; FERRIC OXIDE RED; HYPROMELLOSE, UNSPECIFIED; POLYETHYLENE GLYCOL 3350

HIGHLIGHTS OF PRESCRIBING INFORMATION

These highlights do not include all the information needed to use HYRNUO safely and effectively. See full prescribing information for HYRNUO.
HYRNUO® (sevabertinib) tablets, for oral use
Initial U.S. Approval: 2025

1 INDICATIONS AND USAGE

HYRNUO is a kinase inhibitor indicated for the treatment of adult patients with locally advanced or metastatic non-squamous non-small cell lung cancer (NSCLC) whose tumors have HER2 (ERBB2) tyrosine kinase domain (TKD) activating mutations, as detected by an FDA-approved test, and who have received a prior systemic therapy. (1)

This indication is approved under accelerated approval based on objective response rate (ORR) and duration of response (DOR). Continued approval for this indication may be contingent upon verification and description of clinical benefit in a confirmatory trial.

2 DOSAGE AND ADMINISTRATION

- Select patients for treatment with HYRNUO based on the presence of HER2 (ERBB2) TKD activating mutations. (2.1)
- Recommended Dosage: 20 mg orally twice daily with food until disease progression or unacceptable toxicity. Swallow tablets whole. (2.2)

3 DOSAGE FORMS AND STRENGTHS

Tablets: 10 mg of sevabertinib. (3)

4 CONTRAINDICATIONS

None. (4)

5 WARNINGS AND PRECAUTIONS

- Diarrhea: At the first sign of diarrhea or increased bowel movement frequency, instruct patients to start an antidiarrheal treatment, and to increase their fluid and electrolyte intake. Interrupt, reduce the dose, or permanently discontinue HYRNUO based on severity. (5.1)
- Hepatotoxicity: Monitor liver function tests including ALT, AST, and total bilirubin at baseline prior to administration of HYRNUO, every 2 weeks during the first month, and then monthly thereafter as clinically indicated, with more frequent testing in patients who develop transaminase elevations. Interrupt, reduce the dose, or permanently discontinue HYRNUO based on severity. (5.2)
- Interstitial Lung Disease (ILD)/Pneumonitis: Monitor patients for new or worsening symptoms indicative of ILD/pneumonitis (e.g., dyspnea, cough, fever). Discontinue HYRNUO upon confirmation of ILD/pneumonitis. (5.3)
- Ocular Toxicity: Promptly refer patients presenting with new or worsening eye symptoms to an ophthalmologist. Interrupt, reduce the dose or permanently discontinue HYRNUO based on severity. (5.4)
- Pancreatic Enzyme Elevation: Monitor amylase and lipase regularly during treatment. Interrupt, reduce the dose, or permanently discontinue HYRNUO based on severity. (5.5)
- Embryo-fetal toxicity: Can cause fetal harm. Advise patients of the potential risk to a fetus and to use effective contraception. (5.6, 8.1, 8.3)

6 ADVERSE REACTIONS

- Most common adverse reactions (>20%): diarrhea, rash, paronychia, stomatitis, and nausea.
- Most common Grade 3 or 4 laboratory abnormalities (≥2%): decreased potassium, increased lipase, decreased lymphocyte count, decreased sodium, increased amylase, increased ALT, and increased AST. (6.1)

To report SUSPECTED ADVERSE REACTIONS, contact Bayer HealthCare Pharmaceuticals Inc. at 1-888-842-2937 or FDA at 1-800-FDA-1088 or www.fda.gov/medwatch.

7 DRUG INTERACTIONS

- Strong CYP3A Inhibitors: Avoid concomitant use with strong CYP3A inhibitors. If concomitant use cannot be avoided, reduce HYRNUO dosage. (2.4, 7.1).
- Moderate CYP3A Inhibitors: Monitor patients for increased HYRNUO-associated adverse reactions (2.3, 7.1)
- Strong and Moderate CYP3A Inducers: Avoid concomitant use with strong or moderate CYP3A inducers. (7.1)
- Certain CYP3A Substrates: Avoid concomitant use with CYP3A substrates where minimal increases in concentration may lead to serious adverse reactions unless otherwise recommended in the Prescribing Information of the CYP3A substrate. (7.2)
- Certain P-gp Substrates: Refer to the Prescribing Information for P-gp substrates where minimal increases in concentration may lead to serious adverse reactions (7.2)

8 USE IN SPECIFIC POPULATIONS

- Lactation: Advise not to breastfeed. (8.2)

FULL PRESCRIBING INFORMATION

1 INDICATIONS AND USAGE

HYRNUO is indicated for the treatment of adult patients with locally advanced or metastatic non-squamous non-small cell lung cancer (NSCLC) whose tumors have HER2 (ERBB2) tyrosine kinase domain (TKD) activating mutations, as detected by an FDA-approved test [see Dosage and Administration (2.1)], and who have received a prior systemic therapy.

This indication is approved under accelerated approval based on objective response rate (ORR) and duration of response (DOR) [see Clinical Studies (14)]. Continued approval for this indication may be contingent upon verification and description of clinical benefit in a confirmatory trial.

2 DOSAGE AND ADMINISTRATION

2.1 Patient Selection

Select patients for treatment of locally advanced or metastatic non-squamous NSCLC based on the presence of HER2 (ERBB2) TKD activating mutations in tumor specimens [see Clinical Studies (14)].

Information on FDA-approved tests is available at http://www.fda.gov/CompanionDiagnostics.

2.2 Recommended Dosage

The recommended dosage of HYRNUO is 20 mg orally twice daily with food, until disease progression or unacceptable toxicity [see Clinical Pharmacology (12.3)]. Swallow tablets whole. Do not cut, crush, or chew tablets.

Missed Dose

If a dose is missed, take the missed dose as soon as you remember prior to the next scheduled dose. Do not take 2 doses at the same time to make up for the missed dose.

Vomited Dose

If a dose is vomited, do not take an additional dose. Resume dosing at the next scheduled time.

2.3 Dosage Modifications for Adverse Reactions

The recommended dosage reductions for adverse reactions are provided in Table 1.

Table 1: Recommended HYRNUO Dosage Reductions for Adverse Reactions
Dose Reduction | Dosage Modification
First | 10 mg twice daily
Second | 10 mg once daily
Permanently discontinue HYRNUO in patients who are unable to tolerate 10 mg once daily.

The recommended dosage modifications for adverse reactions are provided in Table 2.

Table 2: Recommended HYRNUO Dosage Modifications for Adverse Reactions
Adverse Reaction | Severity [Grades based on National Cancer Institute Common Terminology Criteria for Adverse Events (NCI CTCAE) Version 5.0.] | Dosage Modification
Diarrhea [see Warnings and Precautions (5.1)] | Intolerable Grade 2 or Grade 3 | - Interrupt HYRNUO until recovery to Grade ≤1. - Resume HYRNUO at the same dose or the next lower dose. - For recurrence, resume HYRNUO at the next lower dose.
Diarrhea [see Warnings and Precautions (5.1)] | Grade 4 | - Permanently discontinue HYRNUO.
Hepatotoxicity [see Warnings and Precautions (5.2)] | Grade 2, 3 or 4 ALT and/or AST without increased total bilirubin or Grade 3 total bilirubin | - Interrupt HYRNUO until recovery to Grade ≤1 or baseline. - Resume HYRNUO at the next lower dose.
Hepatotoxicity [see Warnings and Precautions (5.2)] | ALT or AST ≥ 3× ULN with total bilirubin ≥ 2× ULN or Grade 4 total bilirubin | - Permanently discontinue HYRNUO.
Interstitial lung disease (ILD)/pneumonitis [see Warnings and Precautions (5.3)] | Any Grade | - Permanently discontinue HYRNUO.
Ocular toxicity [see Warnings and Precautions (5.4)] | Grade 2 | - Interrupt HYRNUO until recovery to Grade ≤1. - Resume HYRNUO at the next lower dose. - For recurrence, permanently discontinue HYRNUO.
Ocular toxicity [see Warnings and Precautions (5.4)] | Grade 3 or Grade 4 | - Permanently discontinue HYRNUO.
Pancreatic Enzyme Elevation [see Warnings and Precautions (5.5)] | Grade 3 | - Interrupt HYRNUO until recovery to Grade ≤2 or baseline. - Resume HYRNUO at the next lower dose.
Pancreatic Enzyme Elevation [see Warnings and Precautions (5.5)] | Grade 4 | - Permanently discontinue HYRNUO.
Other adverse reactions [see Adverse Reactions (6.1)] | Intolerable or recurrent Grade 2 or Grade 3 | - Interrupt HYRNUO until recovery to Grade ≤1. - Resume HYRNUO at the same dose or the next lower dose. - For recurrence, resume HYRNUO at the next lower dose.
Other adverse reactions [see Adverse Reactions (6.1)] | Grade 4 | Permanently discontinue HYRNUO.

2.4 Dosage Modifications for Strong CYP3A Inhibitors

Avoid concomitant use of strong CYP3A inhibitors. If concomitant use cannot be avoided, reduce HYRNUO dosage as shown in Table 3. After the CYP3A inhibitor has been discontinued for 3 to 5 elimination half-lives, resume the HYRNUO dosage that was used prior to initiating the inhibitor [see Drug Interactions (7.1)].

Table 3: Recommended HYRNUO Dosage Modifications for Concomitant Use with Strong CYP3A Inhibitors
Current Dosage | Recommended Dosage
20 mg twice daily | 10 mg twice daily
10 mg twice daily | 10 mg once daily
10 mg once daily | Withhold HYRNUO until strong CYP3A inhibitor is discontinued

3 DOSAGE FORMS AND STRENGTHS

Tablets: red brown film-coated, round, biconvex tablets debossed with "SE" on one side and "10" on the other side containing 10 mg of sevabertinib.

4 CONTRAINDICATIONS

None.

5 WARNINGS AND PRECAUTIONS

5.1 Diarrhea

HYRNUO can cause severe diarrhea that can lead to dehydration and electrolyte imbalances. In the pooled safety population [see Adverse Reactions (6.1)], diarrhea was reported in 86% of patients who received HYRNUO including Grade 3 in 15%. The median time to first onset of any grade diarrhea was four days. Dosage interruptions occurred in 15% of patients, and dose reductions occurred in 12% of patients.

At the first sign of diarrhea or increased bowel movement frequency, instruct patients to start an antidiarrheal treatment (e.g., loperamide [refer to full Prescribing Information]), and to increase their fluid and electrolyte intake. Interrupt, reduce the dose, or permanently discontinue HYRNUO based on severity [see Dosage and Administration (2.3)].

5.2 Hepatotoxicity

HYRNUO can cause severe hepatotoxicity characterized by elevations of liver function tests. In the pooled safety population [see Adverse Reactions (6.1)], based on adverse reaction data, hepatotoxicity occurred in 24% of patients treated with HYRNUO including 3% Grade 3. Based on laboratory data, 35% of patients treated with HYRNUO experienced increased alanine aminotransferase (ALT), including 2.3% Grade 3. Increased aspartate aminotransferase (AST) occurred in 35% of patients treated with HYRNUO, including 2.3% Grade 3. Increased bilirubin occurred in 12% of patients treated with HYRNUO. The median time to first onset of AST or ALT elevation was 1.4 (range 0.2 to 14.5) months. HYRNUO was interrupted for an adverse reaction of hepatotoxicity in 4.1% of patients, the dose was reduced in 4.1% and permanently discontinued in 0.4%.

Monitor liver function tests including ALT, AST, and total bilirubin at baseline prior to the first administration of HYRNUO, every 2 weeks for the first month, and then monthly thereafter as clinically indicated, with more frequent testing in patients who develop transaminase elevations. Interrupt, reduce the dose, or permanently discontinue HYRNUO based on the severity of the adverse reaction [see Dosage and Administration (2.3)].

5.3 Interstitial Lung Disease/Pneumonitis

HYRNUO can cause severe interstitial lung disease (ILD)/pneumonitis. In the pooled safety population [see Adverse Reactions (6.1)], ILD/pneumonitis occurred in two patients (0.7%) treated with HYRNUO, including 0.4% Grade 3. One patient required interruption of HYRNUO.

Monitor patients for new or worsening symptoms indicative of ILD/pneumonitis (e.g., dyspnea, cough, fever). Discontinue HYRNUO upon confirmation of ILD/pneumonitis [see Dosage and Administration (2.3)].

5.4 Ocular Toxicity

HYRNUO can cause ocular toxicity. In the pooled safety population [see Adverse Reactions (6.1)], ocular toxicity occurred in 14% of patients treated with HYRNUO, including 11% Grade 1, 2.6% Grade 2 and 0.4% Grade 3 (one case of corneal epithelial microcysts with temporary unilateral blindness).

Promptly refer patients presenting with new or worsening eye symptoms to an ophthalmologist. Interrupt, reduce the dose or permanently discontinue HYRNUO based on severity [see Dosage and Administration (2.3)].

5.5 Pancreatic Enzyme Elevation

HYRNUO can cause elevations of amylase and lipase levels. In the pooled safety population [see Adverse Reactions (6.1)], based on laboratory data, increased amylase occurred in 32% of patients treated with HYRNUO, including 3.2% Grade 3 or 4. Increased lipase elevation occurred in 40% of patients treated with HYRNUO, including 10% Grade 3 or 4. Two patients (0.7%) required interruption of HYRNUO due to increased lipase and 3 (1.1%) required interruption of HYRNUO due to increased amylase. The median time to onset of increased amylase/lipase was 1.4 months (range 0.2 to 17 months).

Monitor amylase and lipase regularly during treatment with HYRNUO. Interrupt, reduce the dose, or permanently discontinue HYRNUO based on severity [see Dosage and Administration (2.3)].

5.6 Embryo-fetal toxicity

Based on findings from animal studies and its mechanism of action, HYRNUO can cause fetal harm when administered to a pregnant woman. In embryo-fetal development studies, oral administration of sevabertinib to pregnant rats during the period of organogenesis resulted in alterations to growth at maternal exposures ≥0.18 times the human exposure based on area under the curve (AUC) at the clinical dose of 20 mg twice daily. Animal studies with disrupted or depleted HER2/EGFR and in vitro assays have demonstrated that inhibition of HER2 and/or EGFR results in structural abnormalities, alteration to growth, and embryo-fetal and infant mortality.

Advise pregnant women and females of reproductive potential of the potential risk to a fetus. Advise females of reproductive potential to use effective contraception during treatment with HYRNUO and for 1 week after the last dose. Advise male patients with female partners of reproductive potential to use effective contraception during treatment with HYRNUO and for 1 week after the last dose [see Use in Specific Populations (8.1, 8.3)].

6 ADVERSE REACTIONS

The following clinically significant adverse reactions are discussed in greater detail in other sections of the labeling:

- Diarrhea [see Warnings and Precautions (5.1)]
- Hepatotoxicity [see Warnings and Precautions (5.2)]
- Interstitial Lung Disease (ILD)/Pneumonitis [see Warnings and Precautions (5.3)]
- Ocular Toxicity [see Warnings and Precautions (5.4)]
- Pancreatic Enzyme Elevation [see Warnings and Precautions (5.5)]

6.1 Clinical Trial Experience

Because clinical trials are conducted under widely varying conditions, adverse reaction rates observed in the clinical trials of a drug cannot be directly compared to rates in the clinical trials of another drug and may not reflect the rates observed in practice.

The pooled safety population in the WARNINGS AND PRECAUTIONS reflects exposure to HYRNUO at 20 mg orally twice daily in 268 patients with locally advanced or metastatic NSCLC harboring HER2 and/or other mutations from the SOHO-01 study [see Clinical Studies (14)]. Among 268 patients who received HYRNUO, 35% were exposed for greater than 6 months and 12% were exposed for greater than 1 year. In this pooled safety population, the most common (>20%) adverse reactions were diarrhea, rash, stomatitis, and paronychia. The most common (≥2%) Grade 3 or 4 laboratory abnormalities were decreased potassium, increased lipase, decreased lymphocyte count, decreased sodium, increased amylase, increased ALT, and increased AST.

The safety of HYRNUO at 20 mg orally twice daily was evaluated in 136 patients with locally advanced or metastatic NSCLC harboring HER2 activating mutations who had received prior systemic therapy in the SOHO-01 study [see Clinical Studies (14)]. Among 136 patients who received HYRNUO, 46% were exposed greater than 6 months and 15% were exposed for greater than 1 year. The median age of patients who received HYRNUO was 62 years (range: 29 to 91); 63% female; 65% Asian, 27% White, 3.7% Black or African American; and 2.2% were of Hispanic or Latino ethnicity.

The most common adverse reactions (>20%) in patients who received HYRNUO were diarrhea, rash, paronychia, stomatitis, and nausea. The most common Grade 3 or 4 laboratory abnormalities (≥2%) were potassium decreased, lipase increased, lymphocyte count decreased, sodium decreased, amylase increased, aspartate aminotransferase (AST) increased, and alanine aminotransferase (ALT) increased.

Serious adverse reactions occurred in 31% of patients who received HYRNUO. Serious adverse reactions in ≥2% of patients were diarrhea (6%), pneumonia (3.7%), dyspnea (2.2%), and pleural effusion (2.2%).

Permanent discontinuation of HYRNUO due to an adverse reaction occurred in 3.7% of patients. Adverse reactions which resulted in permanent discontinuation were corneal epithelial microcysts, hepatic function abnormal, electrocardiogram QT prolonged, pain in extremity and dyspnea (0.7%, 1 patient each).

Dosage interruptions of HYRNUO due to an adverse reaction occurred in 46% of patients. Adverse reactions which resulted in dosage interruptions in >3% of patients were diarrhea, hypokalemia, nausea, decreased appetite, and pneumonia.

Dose reductions of HYRNUO due to adverse reactions occurred in 28% of patients. Adverse reactions which resulted in dose reductions in >2% of patients were diarrhea, rash, and hypokalemia.

Table 4 summarizes the adverse reactions in SOHO-01 (Groups D and E).

Table 4: Adverse Reactions (≥10%) in Patients with NSCLC with HER2 Activating Mutations Who Received HYRNUO in SOHO-01 (Groups D and E)
Adverse Reaction [Graded per NCI CTCAE version 5.] | HYRNUO N = 136
Adverse Reaction [Graded per NCI CTCAE version 5.] | All Grades (%) | Grade 3 or 4 [All were Grade 3, except for dyspnea (0.7%, Grade 4).] (%)
Gastrointestinal disorders
Diarrhea [Includes diarrhea, enterocolitis.] | 87 | 18
Stomatitis [Includes cheilitis, mouth ulceration, mucosal inflammation, stomatitis.] | 29 | 1.5
Nausea | 21 | 1.5
Vomiting | 15 | 2.2
Abdominal pain [Includes abdominal pain, abdominal pain upper.] | 10 | 0
Skin and subcutaneous tissue disorders
Rash [Includes dermatitis acneiform, eczema, eczema asteatotic, palmar-plantar erythrodysaesthesia syndrome, rash, rash erythematous, rash maculopapular, rash pruritic, rash pustular, skin exfoliation.] | 66 | 1.5
Paronychia [Includes ingrowing nail, nail disorder, onychoclasis, onycholysis, onychomadesis, paronychia.] | 33 | 0
Dry skin [Includes dry skin, xeroderma.] | 20 | 0
Pruritus | 14 | 1.5
Metabolism and nutrition disorders
Decreased appetite | 18 | 2.9
Investigations
Weight decreased | 19 | 0.7
General disorders and administration site conditions
Fatigue [Includes asthenia, fatigue.] | 13 | 0.7
Eye disorders
Ocular toxicity [Includes blindness unilateral, cataract, conjunctivitis, conjunctivitis allergic, corneal epithelial microcysts, dry eye, eye discharge, eye pain, lacrimation increased, ocular hyperemia, ocular hypertension, ocular toxicity, vision blurred, visual acuity reduced, visual impairment, xerophthalmia.] | 16 | 0.7
Respiratory disorders
Dyspnea [Includes dyspnea, dyspnea exertional.] | 10 | 1.5

Clinically relevant adverse reactions in <10% of patients who received HYRNUO included edema (8%), cardiac arrhythmia (6%; includes arrhythmia, atrioventricular block complete, electrocardiogram QT prolonged, sinus bradycardia, sinus tachycardia, supraventricular extrasystoles, supraventricular tachycardia, tachycardia) and alopecia (3.7%).

Table 5 summarizes the laboratory abnormalities observed in SOHO-01 (Groups D and E).

Table 5: Select Laboratory Abnormalities (≥20%) That Worsened from Baseline in Patients with NSCLC with HER2 Activating Mutations in SOHO-01 (Groups D and E)
Laboratory Abnormality | HYRNUO N=136 [The denominator used to calculate the rate varied from 103 to 135 based on the number of patients with a baseline value and at least one post-treatment value.]
Laboratory Abnormality | All Grades (%) [Graded per NCI CTCAE version 5 using only numeric values.] | Grade 3 or 4 [All were Grade 3, except for calcium decreased (0.7%, Grade 4) and amylase increased (1.5%; Grade 4)] (%)
Hematology
Hemoglobin decreased | 47 | 1.5
Lymphocyte count decreased | 32 | 6
White blood cell decreased | 21 | 0.7
Chemistry
Lipase increased | 48 | 12
Potassium decreased | 45 | 13
Aspartate aminotransferase increased | 41 | 3
Magnesium decreased | 40 | 0
Alanine aminotransferase increased | 37 | 3
Glucose increased [Graded per NCI CTCAE version 4.03 using only numeric values.] | 36 | 0.7
Albumin decreased | 32 | 1.5
Amylase increased | 31 | 3.8
Calcium decreased | 28 | 1.5
Creatinine increased | 27 | 0
Sodium decreased | 26 | 4.4
Alkaline phosphatase increased | 24 | 0
Triglycerides increased | 22 | 0

Laboratory abnormalities in <20% of patients who received HYRNUO include blood bilirubin increased (14%; all were Grades 1 and 2).

7 DRUG INTERACTIONS

7.1 Effect of Other Drugs on HYRNUO

Table 6 describes drug interactions where concomitant use of another drug affects HYRNUO.

Table 6: Drug Interactions that Affect HYRNUO
Strong and Moderate CYP3A Inhibitors
Prevention or management | Strong CYP3A Inhibitors:; - Avoid concomitant use of HYRNUO with strong CYP3A inhibitors. - If concomitant use cannot be avoided, reduce HYRNUO dosage [see Dosage and Administration (2.4)].
 | Moderate CYP3A Inhibitors:; - Monitor patients for increased HYRNUO-associated adverse reactions [see Dosage and Administration (2.3)].
Mechanism and Clinical Effect | - Sevabertinib is a CYP3A substrate. - Concomitant use with a strong or moderate CYP3A inhibitor may increase sevabertinib plasma concentrations [see Clinical Pharmacology (12.3)], which may increase the risk of HYRNUO-associated adverse reactions.
Strong and Moderate CYP3A Inducers
Prevention or management | - Avoid concomitant use of HYRNUO with strong or moderate CYP3A inducers.
Mechanism and Clinical Effect | - Sevabertinib is a CYP3A substrate. - Concomitant use with a strong or moderate CYP3A inducer may decrease sevabertinib plasma concentrations [see Clinical Pharmacology (12.3)], which may decrease the effectiveness of HYRNUO.

7.2 Effects of HYRNUO on Other Drugs

Table 7 describes drug interactions where concomitant use of HYRNUO affects another drug.

Table 7: HYRNUO Drug Interactions that Affect Other Drugs
Certain CYP3A Substrates
Prevention or management | - Avoid concomitant use of HYRNUO with CYP3A substrates where minimal increases in the concentration may lead to serious adverse reactions unless otherwise recommended in the Prescribing Information of the CYP3A substrate.
Mechanism and Clinical Effect | - Sevabertinib is a weak to moderate CYP3A inhibitor. - Sevabertinib increases exposure of CYP3A substrates [see Clinical Pharmacology (12.3)], which may increase the risk of adverse reactions related to these substrates.
Certain P-gp Substrates
Prevention or management | - Refer to the Prescribing Information for P-gp substrates where minimal increases in the concentration may lead to serious adverse reactions.
Mechanism and Clinical Effect | - Sevabertinib is a P-gp inhibitor. - Sevabertinib increases exposure of P-gp substrates [see Clinical Pharmacology (12.3)], which may increase the risk of adverse reactions related to these substrates.
CYP1A1 Substrates
Prevention or management | - Refer to the Prescribing Information of CYP1A1 substrates.
Mechanism and Clinical Impact | - Sevabertinib is an inhibitor of CYP1A1 in vitro. - Sevabertinib may increase exposure of CYP1A1 substrates [see Clinical Pharmacology (12.3)], which may increase the risk of adverse reactions related to these substrates.

8 USE IN SPECIFIC POPULATIONS

8.1 Pregnancy

Risk Summary

Based on findings from animal studies and its mechanism of action [see Clinical Pharmacology (12.1)], HYRNUO can cause fetal harm when administered to a pregnant woman. There are no available data on the use of HYRNUO in pregnant women to inform a drug-associated risk. In embryo-fetal development studies, oral administration of sevabertinib to pregnant rats during the period of organogenesis resulted in alterations to growth at maternal exposures ≥0.18 times the human exposure based on area under the curve (AUC) at the clinical dose of 20 mg twice daily. Animal studies with disrupted or depleted HER2/EGFR and in vitro assays have demonstrated that inhibition of HER2 and/or EGFR results in structural abnormalities, alteration to growth, and embryo-fetal and infant mortality (see Data). Advise pregnant women of the potential risk to a fetus.

In the U.S. general population, the estimated background risk of major birth defects and miscarriage in clinically recognized pregnancies is 2% to 4% and 15% to 20%, respectively.

Data

Animal Data

In embryo-fetal development studies, sevabertinib was administered orally to pregnant rats during the period of organogenesis from gestation day 6 to 17 at doses ranging from 1.5 to 11 mg/kg/day. Sevabertinib treatment resulted in maternal toxicity (reduced body weight and body weight gain) and a reduction in fetal weights at ≥6 mg/kg/day (≥0.18 times the human exposure based on AUC at the clinical dose).

Additional Nonclinical Data

A literature-based assessment of the effects on reproduction in mouse models with disrupted or depleted HER2/EGFR demonstrated that HER2/EGFR is critically important in reproductive and developmental processes including blastocyst implantation, placental development, and embryo-fetal/postnatal survival and development.

In a human-induced pluripotent stem cell-based assay, sevabertinib reduced cardiomyocyte and hepatocyte differentiation markers.

8.2 Lactation

Risk Summary

There are no data on the presence of sevabertinib or its metabolites in human milk or their effects on a breastfed child or on milk production. In rats, sevabertinib or its metabolites are excreted in milk (see Data). Because of the potential for serious adverse reactions in breastfed children from HYRNUO, advise women not to breastfeed during treatment with HYRNUO and for 1 week after the last dose.

Data

Animal Data

Following administration of radiolabeled sevabertinib to lactating rats, sevabertinib or its metabolites were excreted in milk. Sevabertinib-derived radioactivity concentrations were 13- to 26-times higher in milk than in plasma. Approximately 1.3% of the administered dose of sevabertinib-derived radioactivity was excreted into the milk.

8.3 Females and Males of Reproductive Potential

HYRNUO can cause fetal harm when administered to a pregnant woman [see Use in Specific Populations (8.1)].

Pregnancy Testing

Verify pregnancy status in females of reproductive potential prior to initiating HYRNUO.

Contraception

Females

Advise females of reproductive potential to use effective contraception during treatment with HYRNUO and for 1 week after the last dose.

Males

Advise males with female partners of reproductive potential to use effective contraception during treatment with HYRNUO and for 1 week after the last dose.

8.4 Pediatric Use

The safety and effectiveness of HYRNUO have not been established in pediatric patients.

8.5 Geriatric Use

Of the 268 patients with locally advanced or metastatic NSCLC harboring HER2 activating mutations who received HYRNUO at 20 mg twice daily in the SOHO-01study, 43% were 65 years and over and 13% were 75 years and over. No overall differences in effectiveness were observed between these older and younger patients. Grade 3 diarrhea was observed in 23% of patients age ≥75 years and 14% of patients <75 years old.

11 DESCRIPTION

HYRNUO tablets contain sevabertinib, a kinase inhibitor. The chemical name of the drug substance is 3-(3-chloro-2-methoxyanilino)-2-{3-[(2S)-1,4-dioxan-2-ylmethoxy]pyridin-4-yl}-1,5,6,7-tetrahydro-4H-pyrrolo[3,2-c]pyridin-4-one hydrate. The molecular formula is C24H25ClN4O5 (anhydrate) and the molecular weight is 484.93 g/mol (anhydrate).

The structural formula is shown below:

Sevabertinib is present as a non-stoichiometric hydrate as a white to off-white to yellow to pinkish powder. It is slightly soluble in aqueous solution at pH 2, and practically insoluble in aqueous solutions at pH 4.5 and above.

The strength of HYRNUO is based on the anhydrate form. Each HYRNUO tablet for oral use contains 10 mg of sevabertinib. The inactive ingredients are: cellulose microcrystalline, crospovidone, lactose monohydrate, and magnesium stearate. The tablet film coating contains ferric oxide red, hypromellose 5 cP, and macrogol 3350.

12 CLINICAL PHARMACOLOGY

12.1 Mechanism of Action

Sevabertinib is a reversible kinase inhibitor of human epidermal growth factor receptor 2 (HER2). It also exhibits activity against epidermal growth factor receptor (EGFR).

In vitro, sevabertinib inhibited the phosphorylation of HER2 and downstream signaling in cancer cells with HER2 alterations and proliferation of cancer cells overexpressing wild-type HER2 or harboring HER2 mutations.

In vivo, sevabertinib demonstrated antitumor activity in subcutaneous mouse xenograft models derived from human NSCLC tumors harboring an activating HER2 exon 20 mutation.

12.2 Pharmacodynamics

Exposure-Response Relationship

Higher sevabertinib exposure, across the dose range of 10 to 80 mg total daily dose (0.25 to 2 times the recommended dosage), was associated with an increased incidence of diarrhea (all grade and Grade ≥3) and rash.

Cardiac Electrophysiology

At 2 times the maximum recommended dose, a mean increase in the QTc interval >20 ms was not observed.

12.3 Pharmacokinetics

Sevabertinib pharmacokinetics were observed at steady state in patients with advanced NSCLC harboring activating HER2 or EGFR mutations at the approved recommended dosage and are presented as mean (CV%), unless otherwise specified.

Sevabertinib maximum concentration (Cmax) is 902 (45%) ng/mL and total systemic exposure (AUC) is 6,640 (50%) ng*h/mL. Sevabertinib Cmax and AUC increase in a dose-proportional manner across the dose range of 10 mg to 80 mg (0.25 to 2 times the approved recommended total daily dose). Sevabertinib accumulation is approximately 1.7-fold for AUC and 1.3-fold for Cmax at the approved recommended dosage. Steady state is achieved within 3 days.

Absorption

Sevabertinib median (min, max) time to maximum concentrations (Tmax) is approximately 2 hours (0.5, 8.2 hours) after a single dose.

Effect of Food

Sevabertinib Cmax decreases by 56% and AUC decreases by 28% with a high-fat meal (1000 calories, 50% fat) in healthy subjects. No clinically significant differences in sevabertinib pharmacokinetics were observed following administration of a low-fat meal (400 calories, 25% fat).

Distribution

Sevabertinib apparent volume of distribution is 28 L (42%). Sevabertinib plasma protein binding is 95%. The blood-to-plasma concentration ratio is 0.6.

Elimination

Sevabertinib effective half-life is approximately 8 hours (33%) with an apparent clearance of 3.1 L/hour (38%).

Metabolism

Sevabertinib is primarily metabolized by CYP3A (major), CYP1A1 (minor), and glucuronidation (minor).

Excretion

After a single oral dose of radiolabeled sevabertinib 40 mg to healthy subjects, approximately 84% of the dose was recovered in feces (14% unchanged) and approximately 10% in urine (1.3% unchanged).

Specific Populations

No clinically significant effects in the pharmacokinetics of sevabertinib were observed based on age (18 to 91 years), race (27% White, 65% Asian, 2.7% Black/African American), sex, body weight (29 to 155 kg), smoking status, eGFR 30 to < 90 mL/min, or mild hepatic impairment (AST > ULN and total bilirubin ≤ ULN; or total bilirubin >1 to 1.5× ULN and any AST). The effect of severe renal impairment (eGFR 15 to <30 mL/min), end-stage renal disease (eGFR <15 mL/min), moderate hepatic impairment (total bilirubin >1.5 to 3× ULN and any AST) or severe hepatic impairment (total bilirubin > 3× ULN and any AST) on sevabertinib pharmacokinetics is unknown.

Drug Interaction Studies

Clinical Studies

Strong CYP3A Inhibitors: Sevabertinib AUC increased 2.3-fold and Cmax 1.6-fold following concomitant use of itraconazole (strong CYP3A inhibitor) 200 mg once daily.

Strong CYP3A Inducers: Sevabertinib AUC decreased by 79% and Cmax by 57% following concomitant use of carbamazepine (strong CYP3A inducer) 600 mg once daily.

CYP3A Substrates: Midazolam (CYP3A substrate) AUC increased 2-fold and Cmax 1.8-fold following concomitant use of HYRNUO 20 mg twice daily.

P-gp Substrates: Dabigatran etexilate (P-gp substrate) AUC increased 1.4-fold following concomitant use of HYRNUO 20 mg twice daily.

BCRP Substrates: Rosuvastatin (BCRP substrate) AUC increased 1.3-fold and Cmax 1.4-fold following concomitant use of HYRNUO 20 mg twice daily.

Other Drugs: No clinically significant differences in sevabertinib pharmacokinetics were observed when used concomitantly with esomeprazole (proton pump inhibitor).

In Vitro studies

CYP450 Enzymes: Sevabertinib inhibits CYP1A1 and CYP2C8 but does not inhibit CYP2A6, CYP2C9, CYP1A2, CYP2B6, CYP2D6, CYP2C19, or CYP2E1. Sevabertinib does not induce CYP1A2, CYP2B6, or CYP2C19.

Transporter Systems: Sevabertinib is a substrate of P-gp, and BCRP. Sevabertinib inhibits MATE1 and MATE2-K but does not inhibit OATP1B1, OATP1B3, MRP2, OAT1, OAT3, OCT1, or OCT2.

13 NONCLINICAL TOXICOLOGY

13.1 Carcinogenesis, Mutagenesis, Impairment of Fertility

Carcinogenesis

Carcinogenicity studies have not been conducted with sevabertinib.

Mutagenesis

Sevabertinib was not genotoxic in a bacterial reverse mutation (Ames) and an in vitro micronucleus assay, or an in vivo micronucleus assay in rats.

Impairment of Fertility

Fertility studies have not been conducted with sevabertinib.

14 CLINICAL STUDIES

14.1 Locally Advanced or Metastatic Non-squamous NSCLC with HER2 TKD Activating Mutations

The efficacy of HYRNUO was evaluated in SOHO-01 (NCT05099172), an open-label, single-arm, multicenter, multi-cohort clinical study. Eligible patients (Groups D and E) were required to have previously treated locally advanced or metastatic NSCLC with HER2 (ERBB2) activating mutations and have an Eastern Cooperative Oncology Group Performance Status (ECOG PS) of 0 or 1. HER2 (ERBB2) activating mutations were determined in tumor tissue or plasma by local laboratories prior to enrollment. Patients with treated, stable and asymptomatic brain metastases were eligible. Patients with symptomatic CNS metastases, clinically significant cardiac disease, and history of steroid dependent interstitial lung disease (ILD)/pneumonitis were excluded.

Patients received HYRNUO 20 mg orally twice daily until disease progression or unacceptable toxicity. The major efficacy outcomes were confirmed objective response rate (ORR) and duration of response (DOR), as assessed by Blinded Independent Central Review (BICR) using RECIST v1.1.

The efficacy population included 70 patients from Group D, and 52 patients from Group E, with advanced non-squamous NSCLC with HER2 (ERBB2) tyrosine kinase domain (TKD) activating mutations based on prospective local testing. Of the 122 patients in these combined cohorts, tumor tissue samples from 67.2% (82/122) of patients were retrospectively tested using Oncomine™ Dx Target Test (Life Technologies Corporation). While 92.7% (76/82) of samples were positive for HER2 (ERBB2) TKD activating mutations, 7.3% (6/82) were unevaluable, and there were no samples with negative status for HER2 (ERBB2) TKD activating mutations.

NSCLC Previously Treated, Naïve to HER2-Targeted Therapy: Group D

Efficacy was evaluated in 70 patients with locally advanced or metastatic non-squamous NSCLC with HER2 (ERBB2) TKD activating mutations who had received prior systemic therapy but were naïve to therapy targeting HER2 mutations. Baseline demographic and disease characteristics of the efficacy population were: median age 59 years (range 29 to 77 years); 67% female; 70% Asian, 23% White, 1.4% Black or African American, 6% race not reported; 2.9% were of Hispanic or Latino ethnicity. Patients had an ECOG performance status of either 0 (39%) or 1 (61%); 69% were never-smokers, 29% were former smokers and 2.9% were current smokers. All patients had adenocarcinoma histology. Ninety-one percent (91%) of patients had stage IV disease and 20% had stable brain metastases. The median number of prior therapies was 1 (range 1 to 8); 94% of patients received prior platinum-based chemotherapy, 71% received prior immunotherapy, and 69% received both in combination. Among the patients, 70% of patients had a Y772_A775dup (YVMA) exon 20 insertion.

Efficacy results for SOHO-01 Group D are presented in Table 8.

Table 8: Efficacy Results for SOHO-01: Group D [ORR 95% CI calculated using Clopper-Pearson method.]
Efficacy Parameter | HYRNUO N=70
Objective Response Rate (ORR), (95% CI) | 71% (59, 82)
Complete Response | 2.9%
Partial Response | 69%
Duration of Response (DOR) [Observed proportion of responding patients with duration of response beyond landmark time.] | N=50
Median, months (95% CI) [Kaplan-Meier estimate.] | 9.2 (6.3, 15.0)
DOR ≥6 months | 54%
DOR ≥12 months | 18%
CI – Confidence Interval

NSCLC Previously Treated, Including Prior HER2 Targeted Antibody Drug Conjugates (ADCs): Group E

Efficacy was evaluated in 52 patients with locally advanced or metastatic non-squamous NSCLC with HER2 (ERBB2) TKD activating mutations who had received prior systemic therapy including HER2-targeted ADCs.

Baseline demographic and disease characteristics of this efficacy population were: median age 65 years (range 35 to 91 years); 67% female; 62% Asian, 27% White, 6% Black or African American, 6% race not reported; 1.9% were of Hispanic or Latino ethnicity. Patients had an ECOG performance status of either 0 (29%) or 1 (71%); 65% were never-smokers, and 35% were former smokers. All patients had adenocarcinoma histology. Eighty-five percent (85%) of patients had stage IV disease and 29% had stable brain metastases. The median number of prior therapies was 2 (range 1 to 8), 77% of patients received prior platinum-based chemotherapy, 56% received prior immunotherapy, and 56% received both in combination. Among the patients, 77% of patients had a Y772_A775dup (YVMA) exon 20 insertion.

The ORR was 38% (95% CI 25, 53), with 6% of patients having a complete response and 33% of patients having a partial response. The median DOR was 7 months (95% CI 5.6, NE); ranging from 1+ to 17.2+ months based on the observed DOR. The observed proportion of responding patients with DOR of ≥6 months and ≥12 months was 60% and 10%, respectively.

16 HOW SUPPLIED/STORAGE AND HANDLING

How Supplied

HYRNUO 10 mg tablets are supplied as red brown film-coated, round, biconvex tablets debossed with "SE" on one side and "10" on the other side.

HYRNUO tablets are packaged in a HDPE bottle of 120 tablets closed with a child-resistant screw cap.

NDC 50419-397-01

Storage and Handling

Store at 20°C to 25°C (68°F to 77°F); excursions permitted between 15°C to 30°C (59°F to 86°F) [see USP Controlled Room Temperature].

17 PATIENT COUNSELING INFORMATION

Advise the patient to read the FDA-approved patient labeling (Patient Information).

Diarrhea

Inform patients that HYRNUO can cause severe diarrhea. At the first sign of diarrhea or increased bowel movement frequency, instruct patients to start an antidiarrheal treatment (e.g., loperamide), to increase their fluid and electrolyte intake, and to immediately contact their healthcare provider [see Warnings and Precautions (5.1)].

Hepatotoxicity

Inform patients that HYRNUO can cause severe hepatotoxicity characterized by elevations of liver function tests. Inform patients that they will need to undergo lab tests to monitor hepatic function. Advise patients to immediately contact their healthcare provider for signs and symptoms of hepatotoxicity [see Warnings and Precautions (5.2)].

Interstitial Lung Disease (ILD)/Pneumonitis

Inform patients that HYRNUO can cause severe ILD/pneumonitis. Advise patients to immediately contact their healthcare provider for new or worsening respiratory symptoms [see Warnings and Precautions (5.3)].

Ocular Toxicity

Inform patients that HYRNUO can cause ocular toxicity. Advise patients to immediately contact their healthcare provider for new or worsening ocular symptoms [see Warnings and Precautions (5.4)].

Pancreatic Enzyme Elevation

Inform patients that HYRNUO can cause pancreatic enzyme elevation. Inform patients that they will need to undergo lab tests to monitor pancreatic function. Advise patients to immediately contact their healthcare provider for signs and symptoms associated with pancreatic enzyme elevation [see Warnings and Precautions (5.5)].

Embryo-Fetal Toxicity

Advise pregnant women and females of reproductive potential of the potential risk to a fetus. Advise females to inform their healthcare provider of a known or suspected pregnancy [see Warnings and Precautions (5.6) and Use in Specific Populations (8.1, 8.3)].

Advise females of reproductive potential to use effective contraception during treatment with HYRNUO and for 1 week after the last dose [see Use in Specific Populations (8.3)].

Advise male patients with female partners of reproductive potential to use effective contraception during treatment with HYRNUO and for 1 week after the last dose [see Use in Specific Populations (8.3)].

Lactation

Advise women not to breastfeed during treatment with HYRNUO and for 1 week after the last dose [see Use in Specific Populations (8.2)].

Dosage and Administration

- Instruct patients to take HYRNUO twice daily with food. Each tablet should be swallowed whole [see Dosage and Administration (2.2)].
- Instruct patients that if a dose of HYRNUO is missed to take the missed dose as soon as they remember prior to the next scheduled dose. Advise patients not to take two doses together to make up for a missed dose [see Dosage and Administration (2.2)].
- Instruct patients that if a dose of HYRNUO is vomited not to take an additional dose but to take the next dose at the next scheduled time [see Dosage and Administration (2.2)].

Drug Interactions

Advise patients and caregivers to inform their healthcare provider of all concomitant medications, including prescription medicines, over-the-counter drugs, vitamins, and herbal products. Inform patients to avoid St. John's wort, grapefruit, or grapefruit juice while taking HYRNUO [see Drug Interactions (7.1, 7.2)].

Manufactured for:

Bayer HealthCare Pharmaceuticals Inc.
Whippany, NJ 07981 USA

© 2025 Bayer HealthCare Pharmaceuticals Inc.

PATIENT INFORMATION
HYRNUO® (Her noo' oh)
(sevabertinib)
tablets, for oral use

What is HYRNUO?
HYRNUO is a prescription medicine that is used to treat adults with a type of lung cancer called non-small cell lung cancer (NSCLC) that:

- has spread within your chest or to other parts of the body, and
- has a certain abnormal human epidermal growth factor receptor 2 (HER2) gene(s), and
- who have received a previous treatment (systemic therapy).

Your healthcare provider will perform a test to make sure HYRNUO is right for you.
It is not known if HYRNUO is safe and effective in children.

Before taking HYRNUO, tell your healthcare provider about all of your medical conditions, including if you:

- have liver problems.
- have lung or breathing problems other than lung cancer.
- are pregnant or plan to become pregnant. HYRNUO can harm your unborn baby.
  Females who are able to become pregnant:
  - Your healthcare provider will do a pregnancy test before you start treatment with HYRNUO.
  - Use effective birth control (contraception) during treatment and for 1 week after the last dose of HYRNUO.
  - Talk to your healthcare provider about birth control methods that may be right for you.
  - Tell your healthcare provider right away if you become pregnant or think you may be pregnant during your treatment with HYRNUO.
  Males with female partners who are able to become pregnant:
  - Use effective birth control (contraception) during treatment and for 1 week after your last dose of HYRNUO.
  - Talk to your healthcare provider about birth control methods that may be right for you and your partner.
- are breastfeeding or plan to breastfeed. It is not known if HYRNUO passes into breast milk. Do not breastfeed during treatment and for 1 week after the last dose of HYRNUO.

Tell your healthcare provider about all the medicines you take, including prescription and over-the-counter medicines, vitamins, and herbal supplements. HYRNUO may affect the way other medicines work, and other medicines may affect how HYRNUO works.
Know the medicines you take. Keep a list of them with you to show to your healthcare provider and pharmacist when you get a new medicine.

How should I take HYRNUO?

- Take HYRNUO exactly as your healthcare provider tells you.
- Do not change your dose or stop taking HYRNUO unless your healthcare provider tells you to.
- Take HYRNUO 2 times a day with food.
- Swallow HYRNUO tablets whole with a glass of water.
- Do not cut, crush or chew HYRNUO tablets.
- If you miss a dose of HYRNUO, take your prescribed dose as soon as you remember before the next scheduled dose. Do not take 2 doses at the same time to make up for a missed dose.
- If you vomit after taking a dose of HYRNUO, do not make up the dose. Take your next dose at your regularly scheduled time.

What should I avoid while taking HYRNUO?

- Avoid eating grapefruit or drinking grapefruit juice during treatment with HYRNUO. Grapefruit may increase the amount of HYRNUO in your blood.

What are the possible side effects of HYRNUO?
HYRNUO may cause serious side effects, including:

- diarrhea. Diarrhea is common and can be severe during treatment with HYRNUO and usually occurs in the first week of treatment. Diarrhea can cause the loss of body fluids (dehydration) and salts (electrolyte imbalances). At the first signs of diarrhea (loose stool) or increased bowel movements, tell your healthcare provider right away, drink plenty of fluids and start treatment for diarrhea as soon as possible. You should have an anti-diarrhea medicine available before you start taking HYRNUO.
- liver problems. HYRNUO can cause increases in liver blood tests which may be severe. Your healthcare provider will do blood tests to check your liver function before you start taking and during treatment with HYRNUO. Tell your healthcare provider right away if you develop any signs and symptoms of liver problems including:

- yellowing of the skin or white part of your eyes (jaundice)
- dark urine
- pale stools
- tiredness or weakness

- nausea or vomiting
- loss of appetite
- pain on the upper right side of your stomach

- lung problems. HYRNUO may cause severe lung problems. Tell your healthcare provider right away if you develop any new or worsening symptoms of lung problems during treatment with HYRNUO, including:

- cough

- fever

- shortness of breath or trouble breathing

- eye problems. HYRNUO can cause eye problems that can lead to temporary loss of vision. Your healthcare provider may send you to see an eye specialist (ophthalmologist) if you develop new or worsening eye problems during treatment with HYRNUO.
- pancreas problems. HYRNUO may cause increases in certain pancreatic lab tests (amylase and lipase). Your healthcare provider will do blood tests to check your pancreatic function before and during treatment with HYRNUO. Tell your healthcare provider right away if you develop any signs and symptoms of pancreas problems, including:
  - upper stomach pain that may spread to your back and get worse with eating
  - weight loss
  - nausea or vomiting

Your healthcare provider may change your dose, temporarily stop, or completely stop your treatment with HYRNUO if you have certain side effects.

The most common side effects of HYRNUO include:

- rash
- nail problems including infection and inflammation
- mouth sores
- nausea

- changes in certain blood tests

These are not all of the possible side effects of HYRNUO.
Call your doctor for medical advice about side effects. You may report side effects to FDA at 1-800-FDA-1088.

How should I store HYRNUO?

- Store HYRNUO at room temperature between 68°F to 77°F (20°C to 25°C).
- HYRNUO comes in a child-resistant container.

Keep HYRNUO and all medicines out of the reach of children.

General information about the safe and effective use of HYRNUO.
Medicines are sometimes prescribed for purposes other than those listed in a Patient Information leaflet. Do not use HYRNUO for a condition for which it was not prescribed. Do not give HYRNUO to other people, even if they have the same symptoms that you have. It may harm them. You can ask your healthcare provider or pharmacist for information about HYRNUO that is written for health professionals.

What are the ingredients in HYRNUO?
Active ingredient: sevabertinib
Inactive ingredients: cellulose microcrystalline, crospovidone, lactose monohydrate, and magnesium stearate. Tablet film coating: ferric oxide red, hypromellose 5 cP, and macrogol 3350.

Manufactured for: Bayer HealthCare Pharmaceuticals Inc., Whippany, NJ 07981 USA
For more information, call Bayer HealthCare Pharmaceuticals Inc. at Bayer at 1-888-842-2937 or go to www.HYRNUO-us.com

This Patient Information has been approved by the U.S. Food and Drug Administration.

Issued: 11/2025

PRINCIPAL DISPLAY PANEL - 10 mg Tablet Bottle Label

NDC 50419-397-01

HYRNUO®
(sevabertinib) tablets

10 mg

Rx Only

BAYER

120 film-coated tablets

PRINCIPAL DISPLAY PANEL - 10 mg Tablet Bottle Carton

NDC 50419-397-01
Rx only

HYRNUO®
(sevabertinib) tablets

10 mg

— 120 film-coated tablets
— Oral use

BAYER